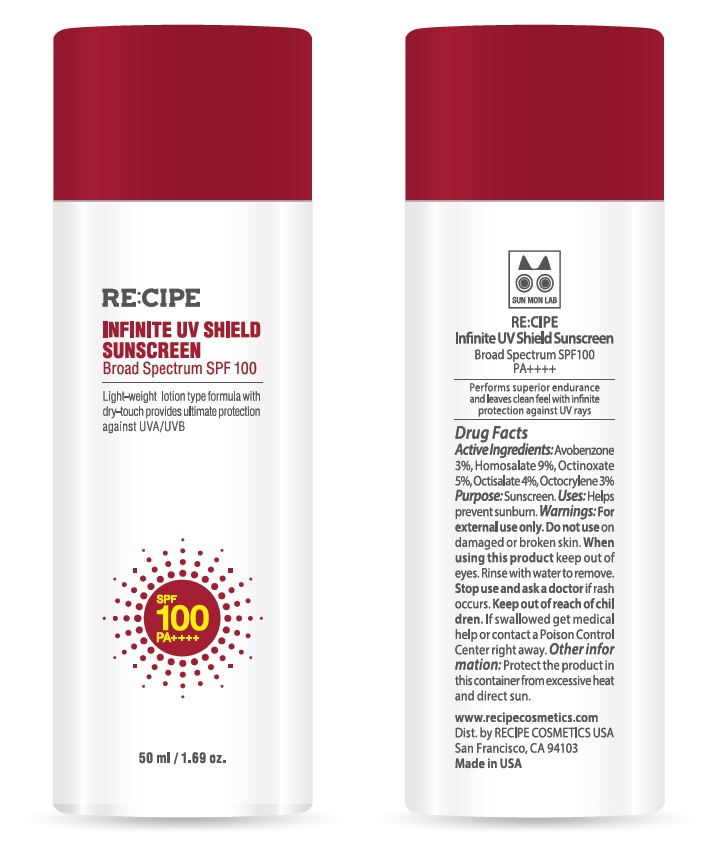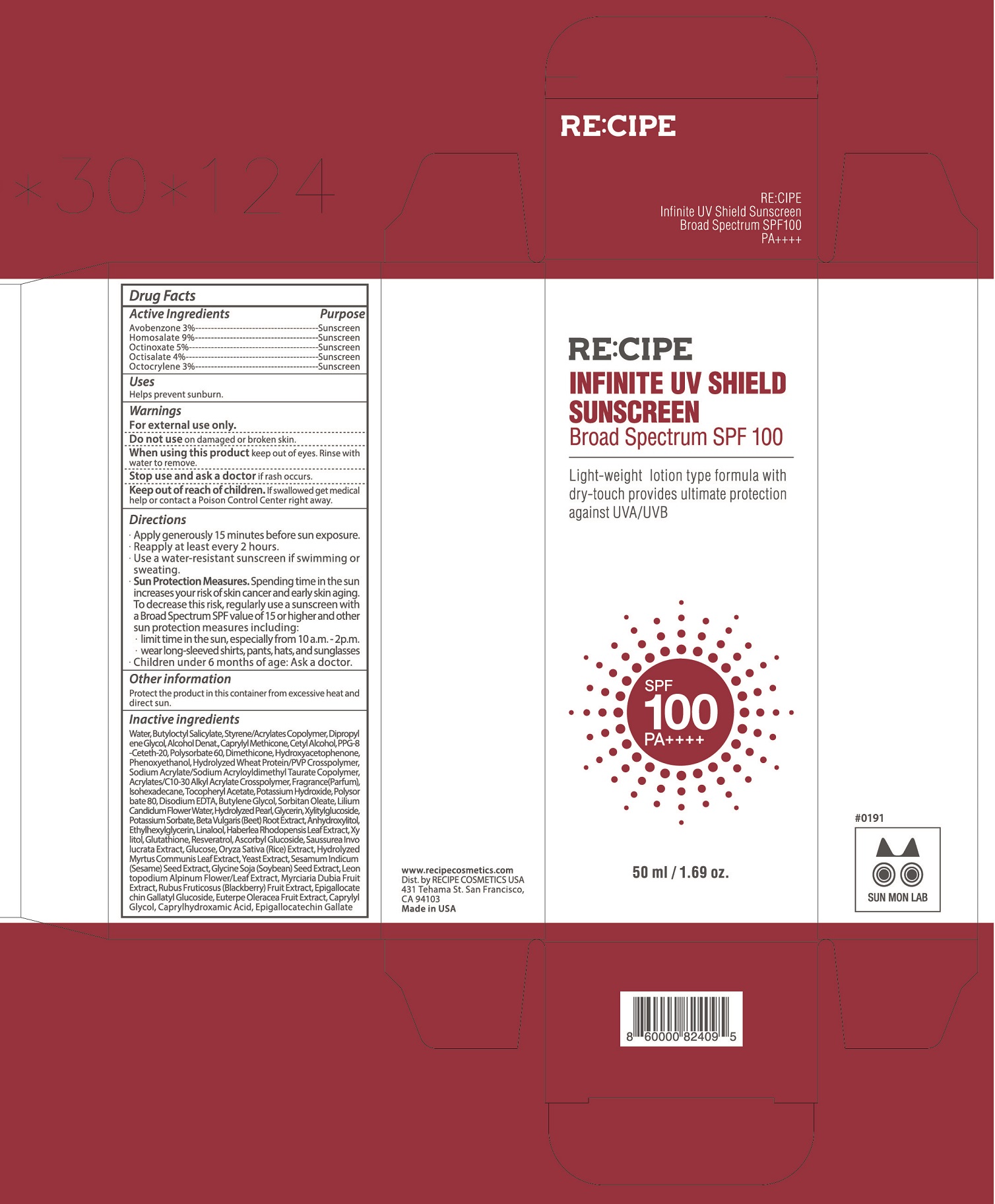 DRUG LABEL: RECIPE Infinite UV Shield Sunscreen Broad Spectrum SPF100
NDC: 68577-161 | Form: LOTION
Manufacturer: COSMAX USA, INC.
Category: otc | Type: HUMAN OTC DRUG LABEL
Date: 20241029

ACTIVE INGREDIENTS: OCTINOXATE 50 mg/1 mL; OCTOCRYLENE 30 mg/1 mL; OCTISALATE 45 mg/1 mL; HOMOSALATE 90 mg/1 mL; AVOBENZONE 30 mg/1 mL
INACTIVE INGREDIENTS: XYLITOL 0.012 mg/1 mL; MYRTUS COMMUNIS LEAF 0.0035 mg/1 mL; CAPRYLHYDROXAMIC ACID 0.0001 mg/1 mL; EPIGALLOCATECHIN GALLATE 0.000025 mg/1 mL; POLYSORBATE 60 10 mg/1 mL; BUTYLOCTYL SALICYLATE 80 mg/1 mL; ETHYLHEXYLGLYCERIN 0.0202 mg/1 mL; ASCORBYL GLUCOSIDE 0.01 mg/1 mL; DIPROPYLENE GLYCOL 50 mg/1 mL; ALCOHOL 30 mg/1 mL; HYDROLYZED WHEAT PROTEIN (ENZYMATIC, 3000 MW) 3.5 mg/1 mL; WATER 435.65785 mg/1 mL; HYDROXYACETOPHENONE 5 mg/1 mL; CARBOMER INTERPOLYMER TYPE A (ALLYL SUCROSE CROSSLINKED) 2 mg/1 mL; ISOHEXADECANE 1.8 mg/1 mL; POTASSIUM HYDROXIDE 1 mg/1 mL; DIMETHICONE 5 mg/1 mL; PHENOXYETHANOL 4.1815 mg/1 mL; CALCIUM CARBONATE 0.0975 mg/1 mL; GLUTATHIONE 0.01 mg/1 mL; RESVERATROL 0.01 mg/1 mL; HABERLEA RHODOPENSIS LEAF 0.0125 mg/1 mL; CETYL ALCOHOL 12 mg/1 mL; GLYCERIN 0.0901 mg/1 mL; POTASSIUM SORBATE 0.04 mg/1 mL; .ALPHA.-TOCOPHEROL ACETATE 1 mg/1 mL; POLYSORBATE 80 0.6 mg/1 mL; SORBITAN MONOOLEATE 0.2 mg/1 mL; LILIUM CANDIDUM FLOWER OIL 0.0995 mg/1 mL; MYRCIARIA DUBIA FRUIT 0.001 mg/1 mL; LEONTOPODIUM NIVALE SUBSP. ALPINUM FLOWERING TOP 0.001 mg/1 mL; ACAI 0.0005 mg/1 mL; BLACKBERRY MESOCARP FREEZE DRIED 0.001 mg/1 mL; YEAST, UNSPECIFIED 0.003 mg/1 mL; CAPRYLYL GLYCOL 0.0002 mg/1 mL; RICE GERM 0.004 mg/1 mL; SESAME SEED 0.003 mg/1 mL; CAPRYLYL TRISILOXANE 30 mg/1 mL; BEET 0.036 mg/1 mL; LINALOOL, (+/-)- 0.018 mg/1 mL; SOYBEAN 0.002 mg/1 mL; SODIUM ACRYLATE/SODIUM ACRYLOYLDIMETHYLTAURATE COPOLYMER (4000000 MW) 3 mg/1 mL; EDETATE DISODIUM ANHYDROUS 0.31 mg/1 mL; BUTYLENE GLYCOL 0.216 mg/1 mL; XYLITYLGLUCOSIDE 0.04 mg/1 mL; ANHYDROXYLITOL 0.028 mg/1 mL; SAUSSUREA INVOLUCRATA WHOLE 0.005 mg/1 mL; ANHYDROUS DEXTROSE 0.004 mg/1 mL

RECIPE Infinite UV Shield Sunscreen Broad Spectrum SPF100

DOSAGE AND ADMINISTRATION

- Apply generously 15 minutes before sun exposure.
- Reapply at least every 2 hours.
- Use a water-resistant sunscreen if swimming or sweating.
- Sun Protection Measures. Spending time in the sun increases your risk of skin cancer and early skin aging. To decrease this risk, regularly use a sunscreen with a Broad Spectrum SPF value of 15 or higher and other sun protection measures including: limit time in the sun, especially from 10 a.m.-2p.m. Wear long-sleeved shirts, pants, hats and sunglasses.
- Children under 6 months of age: ask a doctor.

WARNINGS

For external use only.

INACTIVE INGREDIENT

Water, Butyloctyl Salicylate, Styrene/Acrylates Copolymer, Dipropylene Glycol, Alcohol Denat., Caprylyl Methicone, Cetyl Alcohol, PPG-8-Ceteth-20, Polysorbate 60, Dimethicone, Hydroxyacetophenone, Phenoxyethanol, Hydrolyzed Wheat Protein/PVP Crosspolymer, Sodium Acrylate/Sodium Acryloyldimethyl Taurate Copolymer, Acrylates/C10-30 Alkyl Acrylate Crosspolymer, Fragrance(Parfum), Isohexadecane, Tocopheryl Acetate, Potassium Hydroxide, Polysorbate 80, Disodium EDTA, Butylene Glycol, Sorbitan Oleate, Lilium Candidum Flower Water, Hydrolyzed Pearl, Glycerin, Xylitylglucoside, Potassium Sorbate, Beta Vulgaris (Beet) Root Extract, Anhydroxylitol, Ethylhexylglycerin, Haberlea Rhodopensis Leaf Extract, Xylitol, Glutathione, Resveratrol, Ascorbyl Glucoside, Saussurea Involucrata Extract, Glucose, Oryza Sativa (Rice) Extract, Hydrolyzed Myrtus Communis Leaf Extract, Yeast Extract, Sesamum Indicum (Sesame) Seed Extract, Glycine Soja (Soybean) Seed Extract, Leontopodium Alpinum Flower/Leaf Extract, Myrciaria Dubia Fruit Extract, Rubus Fruticosus (Blackberry) Fruit Extract, Epigallocatechin Gallatyl Glucoside, Euterpe Oleracea Fruit Extract, Caprylyl Glycol, Caprylhydroxamic Acid, Epigallocatechin Gallate

KEEP OUT OF REACH OF CHILDREN

If swallowed get medical help or contact a Poison Control Center right away.

PURPOSE

Sunscreen

ACTIVE INGREDIENT

Avobenzone 3%, Homosalate 9%, Octinoxate 5%, Octisalate 4%, Octocrylene 3%, Purpose: Sunscreen

USES

- Helps prevent sunburn